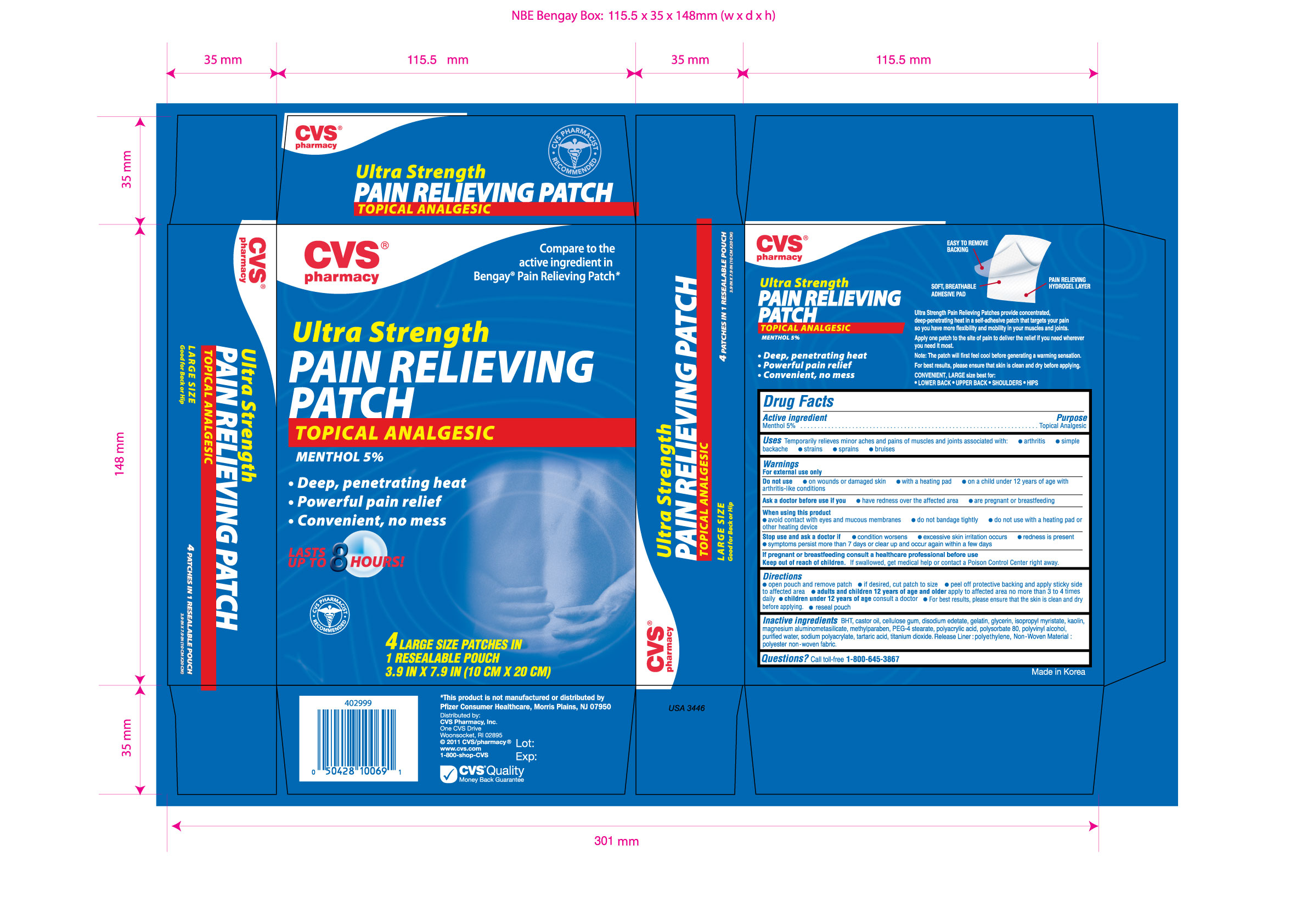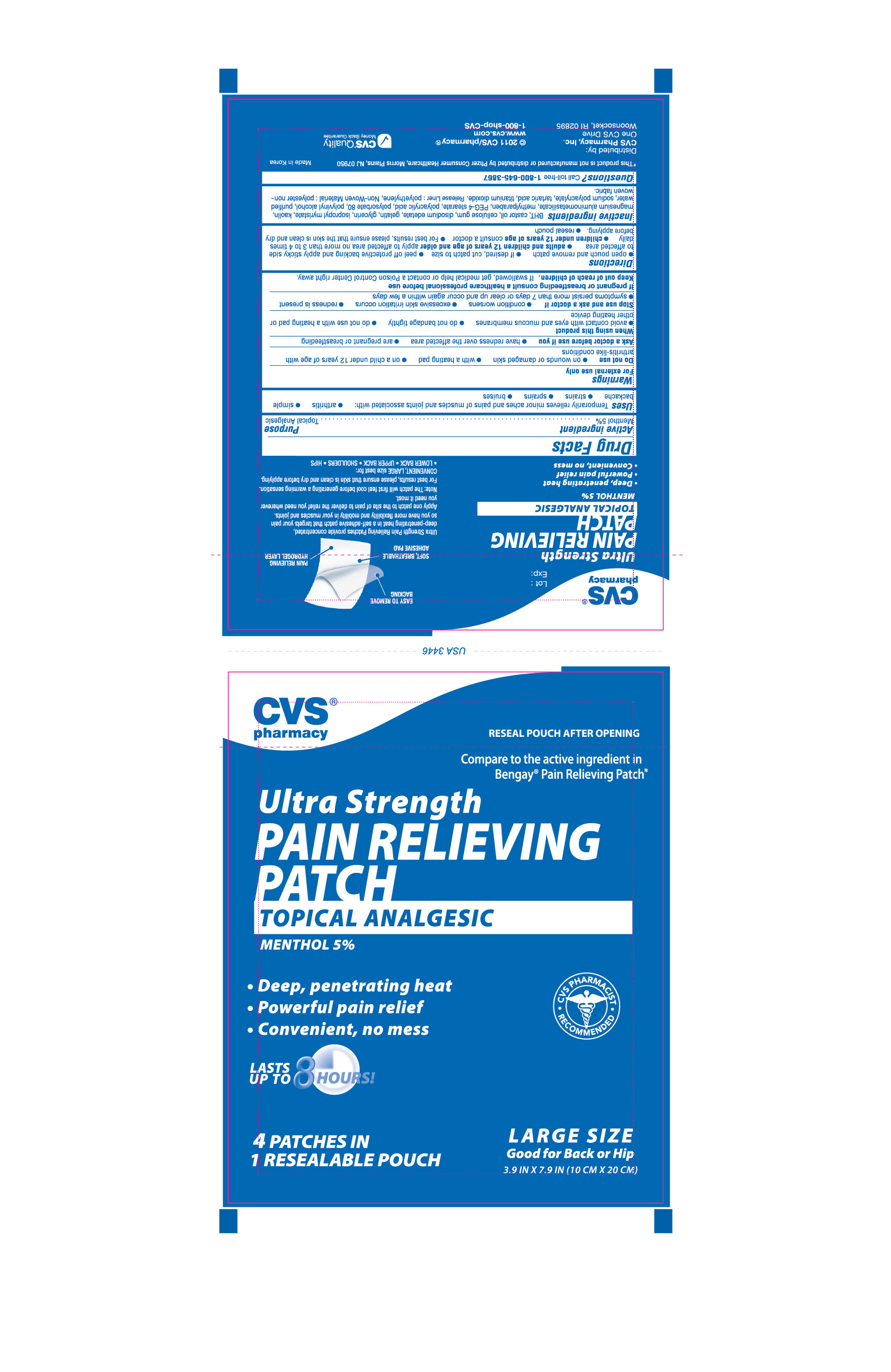 DRUG LABEL: PAIN RELIEVING PATCH ULTRA STRENGTH
  
NDC: 59779-991 | Form: PATCH
Manufacturer: CVS PHARMACY, INC.
Category: otc | Type: HUMAN OTC DRUG LABEL
Date: 20130918

ACTIVE INGREDIENTS: Menthol 50 mg/1 g
INACTIVE INGREDIENTS: Silodrate; Butylated Hydroxytoluene; Castor Oil; Carboxymethylcellulose Sodium; Edetate Disodium; Gelatin; Glycerin; Isopropyl Myristate; Kaolin; Methylparaben; Peg-4 Stearate; Polysorbate 80; Polyvinyl Alcohol; Water; Tartaric Acid; Titanium Dioxide

Menthol 5% (Topical Analgesic)

Active Ingredient
Menthol 5%

Purpose

Topical Analgesic

Uses

Temporarily relieves minor aches and pains of muscles and joints associated with:

- arthritis
- simple backache
- strains
- sprains
- bruises

Warnings

For external use only

Do not use

- on wounds or damaged skin
- with a heating pad
- on a child under 12 years of age with arthritis-like conditions

Ask a doctor before use if you

- have redness over the affected area
- are pregnant or breastfeeding

When using this product

- avoid contact with eyes and mucous membranes
- do not bandage tightly
- do not use with a heating pad or other heating device

Stop using this product if

- condition worsens
- excessive skin irritation occurs
- redness is present
- symptoms persist more than 7 days or clear up and occur again within a few days

If pregnant or breastfeeding consult a healthcare professional before use

Keep out of reach of children. If swallowed, get medical help or contact a Poison Control Center right away.

Directions

- open pouch and remove patch
- if desired, cut patch to size
- peel off protective backing and apply sticky side to affected area
- adults and children 12 years of age and older apply to affected area no more than 3 to 4 times daily
- children under 12 years of age consult a doctor
- For best results, please ensure that the skin is clean and dry before applying
- reseal pouch

INACTIVE INGREDIENT

Inactive Ingredients BHT, castor oil, cellulose gum, disodium edetate, glycerin, isopropyl myristate, kaolin, magnesium aluminometasilicate, methylparaben, PEG-4 stearate, polyacrylic acid, polysorbate 80, polyvinyl alcohol, purified water, sodium polyacrylate, tartaric acid, titanium dioxide. Release Liner: polyethylene, Non-Woven Material: polyester non-woven fabric.

Questions? Call toll-free 1-800-645-3867